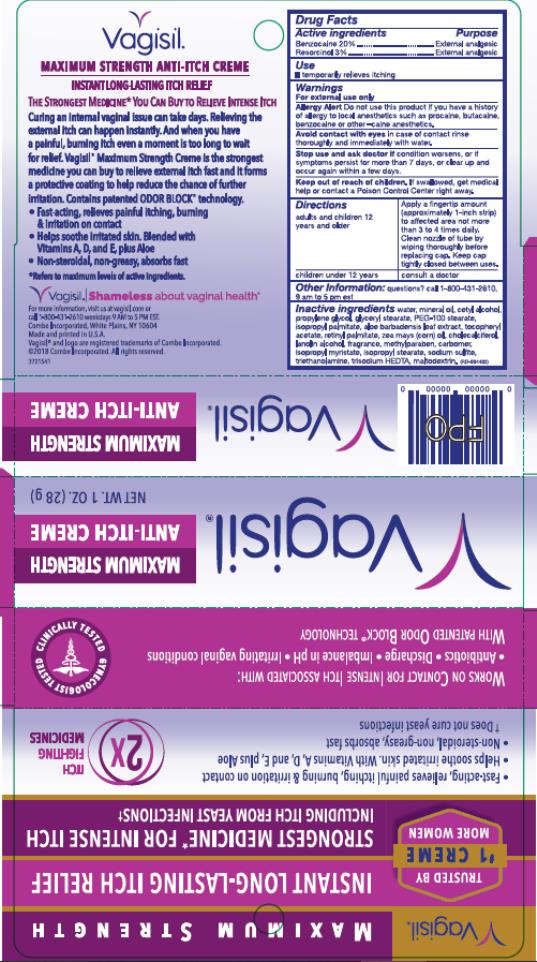 DRUG LABEL: VAGISIL Anti-Itch Medicated Creme Maximum Strength
NDC: 11509-4402 | Form: CREAM
Manufacturer: Combe Incorporated
Category: otc | Type: HUMAN OTC DRUG LABEL
Date: 20241212

ACTIVE INGREDIENTS: BENZOCAINE 200 mg/1 g; RESORCINOL 30 mg/1 g
INACTIVE INGREDIENTS: WATER; MINERAL OIL; CETYL ALCOHOL; PROPYLENE GLYCOL; GLYCERYL MONOSTEARATE; PEG-100 STEARATE; ISOPROPYL PALMITATE; ALOE VERA LEAF; ALPHA-TOCOPHEROL ACETATE; VITAMIN A PALMITATE; CORN OIL; CHOLECALCIFEROL; LANOLIN ALCOHOLS; METHYLPARABEN; CARBOMER HOMOPOLYMER TYPE B (ALLYL PENTAERYTHRITOL CROSSLINKED); ISOPROPYL MYRISTATE; ISOPROPYL STEARATE; SODIUM SULFITE; TROLAMINE; TRISODIUM HEDTA; MALTODEXTRIN

Vagisil Maximum Strength Anti-Itch Creme

VAGISIL Maximum Strength Anti-Itch Creme

Drug Facts

Active ingredient

Benzocaine 20%

Purpose

External analgesic

Active ingredient

Resorcinol 3%

Purpose

External analgesic

Use

temporarily relieves itching

Warnings

For external use only

Allergy Allert

Do not use this product if you have a history of allergy to local anesthetics such as procaine, butacaine, benzocaine or other –caine anesthetics.

Avoid contact with eyes

in case of contact rinse thoroughly and immediately with water.

Stop use and ask doctor if

condition worsens, or if symptoms persist for more than 7 days, or clear up and occur again within a few days

Keep out of reach of children.

If swallowed, get medical help or contact a Poison Control Center right away.

Directions

adults and children 12 years and older | Apply a fingertip amount (approximately 1-inch strip) to affected area not more than 3 to 4 times daily. Clean nozzle of tube by wiping thoroughly before replacing cap. Keep cap tightly closed between uses.
children under 12 years | consult a doctor

Other Information:

questions? call 1-800-431-2610, 9 am to 5 pm est

Inactive ingredients

Water, Mineral Oil, Cetyl Alcohol, Propylene Glycol, Glyceryl Stearate, PEG-100 Stearate, Isopropyl Palmitate, Aloe Barbadensis Leaf Extract, Tocopheryl Acetate, Retinyl Palmitate, Zea Mays (Corn) Oil, Cholecalciferol, Lanolin Alcohol, Fragrance, Methylparaben, Carbomer, Isopropyl Myristate, Isopropyl Stearate, Sodium Sulfite, Triethanolamine, Trisodium HEDTA, Maltodextrin

Principal Display Panel

Vagisil®
Maximum Strength
Anti-Itch Creme

Net Wt. 1 oz. (28 g)